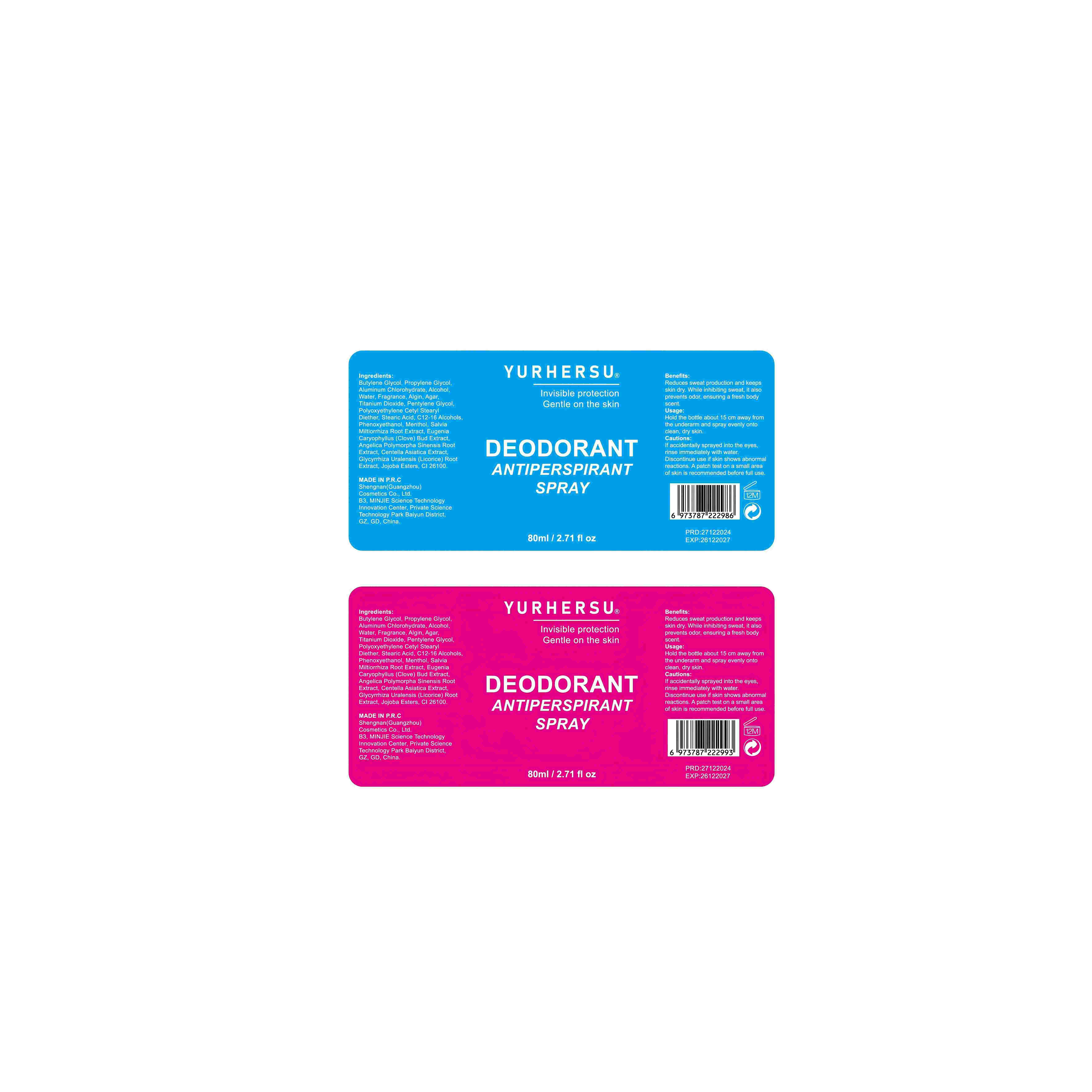 DRUG LABEL: DEODORANTANTIPERSPIRANTSPRAY
NDC: 84019-022 | Form: LIQUID
Manufacturer: Shengnan (Guangzhou) Cosmetics Co., LTD
Category: otc | Type: HUMAN OTC DRUG LABEL
Date: 20241228

ACTIVE INGREDIENTS: ALUMINUM CHLOROHYDRATE 100 mg/1 mL
INACTIVE INGREDIENTS: BUTYLENE GLYCOL; PENTYLENE GLYCOL; TITANIUM DIOXIDE; WATER; STEARIC ACID; ALGIN; AGAR; ALCOHOL

DEODORANT ANTIPERSPIRANT SPRAY 80ml

WARNINGS

Please keep out of reach of children.

PURPOSE

Reduces sweat production and keeps skin dry. While inhibiting sweat, it also prevents odor, ensuring a fresh body scent.

STOP USE

Discontinue use if skin shows abnormalreactions.A patch test on a small areaof skin is recommended before full use.

ACTIVE INGREDIENT

Aluminum Chlorohydrate

WHEN USING

Please keep your skin dry before use to ensure the best results fromthe product.

INACTIVE INGREDIENT

Butylene Glycol
Propylene Glycol
Alcohol
Water
Fragrance
Algin
Agar
Titanium Dioxide
Pentylene Glycol
Polyoxyethylene Cetyl Stearyl Diether
Stearic Acid
C12-16 Alcohols
Phenoxyethanol
Menthol
Salvia Miltiorrhiza Root Extract
Eugenia Caryophyllus (Clove) Bud Extract
Angelica Polymorpha Sinensis Root Extract
Centella Asiatica Extract
Glycyrrhiza Uralensis (Licorice) Root Extract
Jojoba Esters
CI 26100

DOSAGE AND ADMINISTRATION

Apply 2 times a day

INDICATIONS AND USAGE

Hold the bottle about 15 cm away fromthe underarm and spray evenly ontoclean, dry skin.